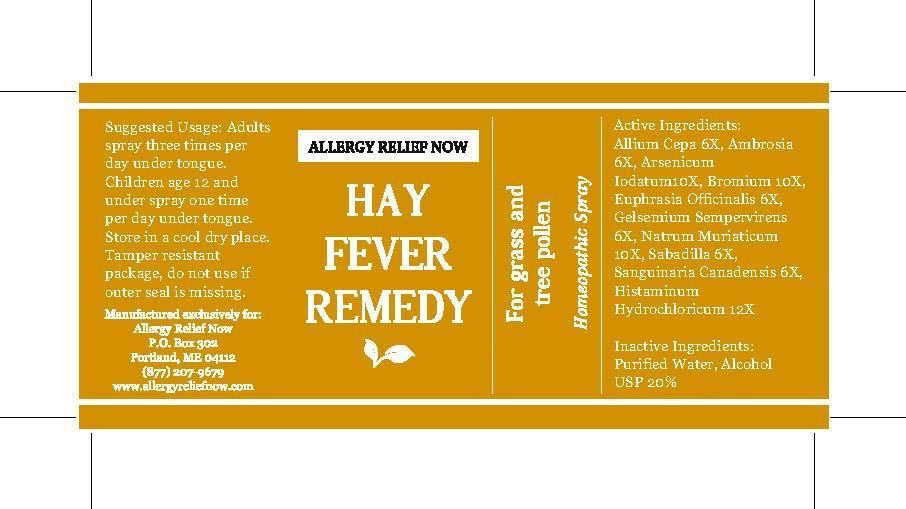 DRUG LABEL: Allergy Relief Now Hay Fever Remedy
NDC: 61727-053 | Form: SPRAY
Manufacturer: Homeocare Laboratories
Category: homeopathic | Type: HUMAN OTC DRUG LABEL
Date: 20140325

ACTIVE INGREDIENTS: ONION 6 [hp_X]/1 [hp_X]; AMBROSIA ARTEMISIIFOLIA 6 [hp_X]/1 [hp_X]; ARSENIC TRIIODIDE 10 [hp_X]/1 [hp_X]; bromine 10 [hp_X]/1 [hp_X]; EUPHRASIA STRICTA 6 [hp_X]/1 [hp_X]; GELSEMIUM SEMPERVIRENS ROOT 6 [hp_X]/1 [hp_X]; SODIUM CHLORIDE 10 [hp_X]/1 [hp_X]; SCHOENOCAULON OFFICINALE SEED 6 [hp_X]/1 [hp_X]; SANGUINARIA CANADENSIS ROOT 6 [hp_X]/1 [hp_X]; HISTAMINE DIHYDROCHLORIDE 12 [hp_X]/1 [hp_X]
INACTIVE INGREDIENTS: WATER; ALCOHOL

Active Ingredients:

Allium Cepa 6X, Ambrosia 6X, Arsenicum Iodatum 10X, Bromium 10X, Euphrasia Officinalis 6X, Gelsemium Sempervirens 6X, Natrum Muriaticum 10X, Sabadilla 6X, Sanguinaria Canadensis 6X, Histaminum Hydrochloricum 12X

Inactive Ingredients:

Purified Water, Alcohol USP 20%

Suggested Usage:

Adults spray three times per day under tongue. Children age 12 and under spray one time per day under tongue. Store in a cool dry place.

INDICATIONS AND USAGE

For grass and tree pollen Homeopathic Spray

Keep out of the reach of children

Do not use if outer seal is missing

Allergy Now Hay Fever Remedy 1 fl oz

Concordia_LabelFinal-hayfever.pdf